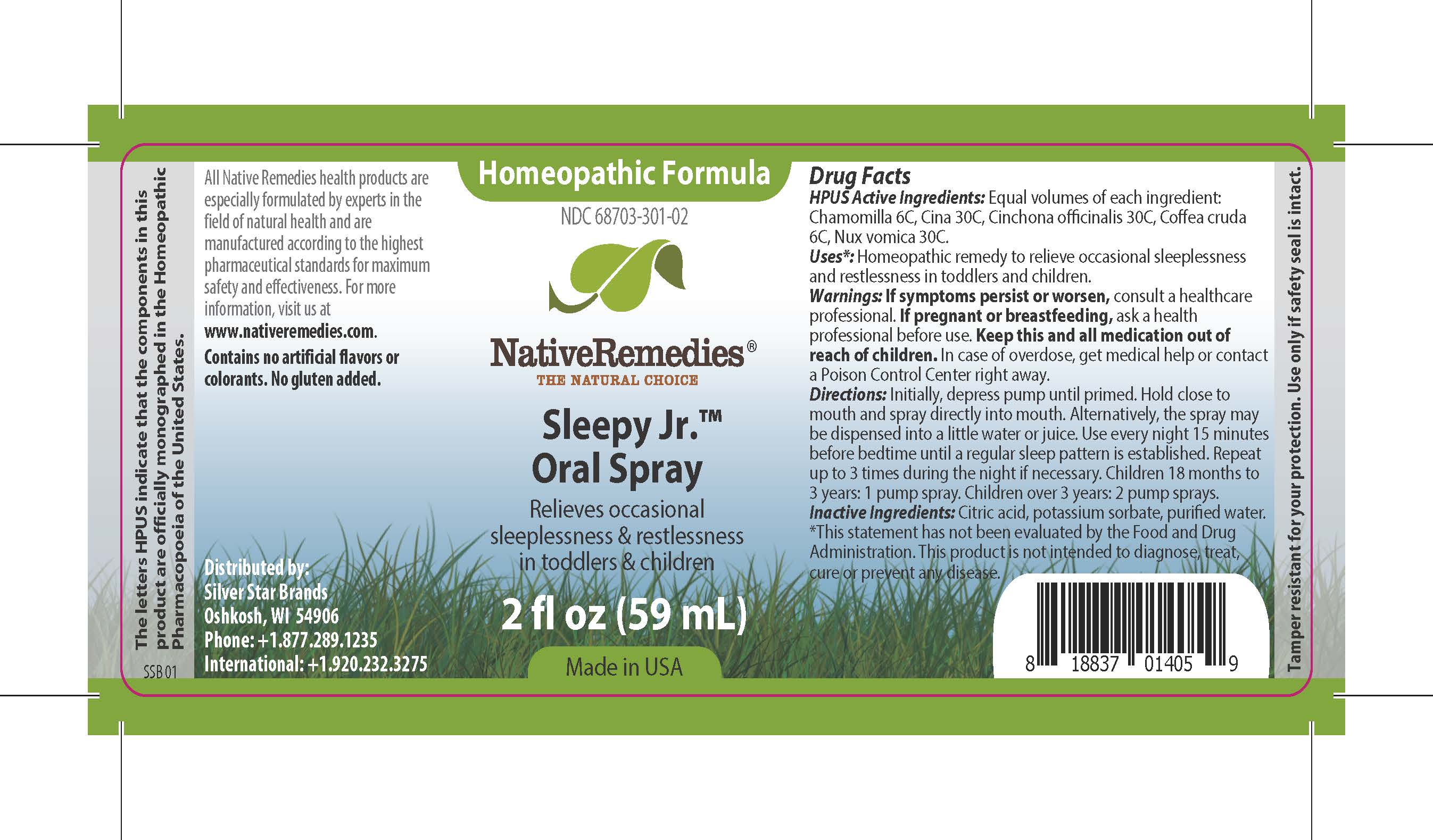 DRUG LABEL: Sleepy Jr
NDC: 68703-301 | Form: SPRAY
Manufacturer: Silver Star Brands
Category: homeopathic | Type: HUMAN OTC DRUG LABEL
Date: 20170413

ACTIVE INGREDIENTS: CINCHONA OFFICINALIS BARK 30 [hp_C]/59 mL; STRYCHNOS NUX-VOMICA SEED 30 [hp_C]/59 mL; MATRICARIA RECUTITA 6 [hp_C]/59 mL; COFFEA ARABICA FRUIT 6 [hp_C]/59 mL; ARTEMISIA CINA FLOWER 30 [hp_C]/59 mL
INACTIVE INGREDIENTS: POTASSIUM SORBATE; WATER; ANHYDROUS CITRIC ACID

NativeRemedies® Sleepy Jr.™

HPUS Active Ingredients:

Equal volumes of each ingredient: Chamomilla 6C, Cina 30C, Cinchona officinalis 30C, Coffea cruda 6C, Nux vomica 30C.

Uses*:

Homeopathic remedy to relieve occasional sleeplessness and restlessness in toddlers and children.

*This statement has not been evaluated by the Food and Drug Administration. This product is not intended to diagnose, treat, cure or prevent any disease.

Warnings:

If symptoms persist or worsen, consult a healthcare professional. If pregnant or breastfeeding, ask a health professional before use. Keep this and all medication out of reach of children. In case of overdose, get medical help or contact a Poison Control Center right away.

Directions:

Initially, depress pump until primed. Hold close to mouth and spray directly into mouth. Alternatively, the spray may be dispensed into a little water or juice. Use every night 15 minutes before bedtime until a regular sleep pattern is established. Repeat up to 3 times during the night if necessary. Children 18 months to 3 years: 1 pump spray. Chidlren over 3 years: 2 pump sprays.

OTHER SAFETY INFORMATION

All Native Remedies health products are especially formulated by experts in the field of natural health and are manufactured according to the highest pharmaceutical standards for maximum safety and effectiveness. Fore more information, visit us at www.nativeremedies.com. Contains no artificial flavors or colorants. No gluten added.

Inactive Ingredients:

Citric acid, potassium sorbate, purified water.

KEEP OUT OF REACH OF CHILDREN

Keep this and all medication out of reach of children. In case of overdose, get medical help or contact a Poison Control Center right away.

PREGNANCY OR BREAST FEEDING

If pregnant or breastfeeding, ask a health professional before use.

PURPOSE

Relieves occasional sleeplessness & restlessness in toddlers & children